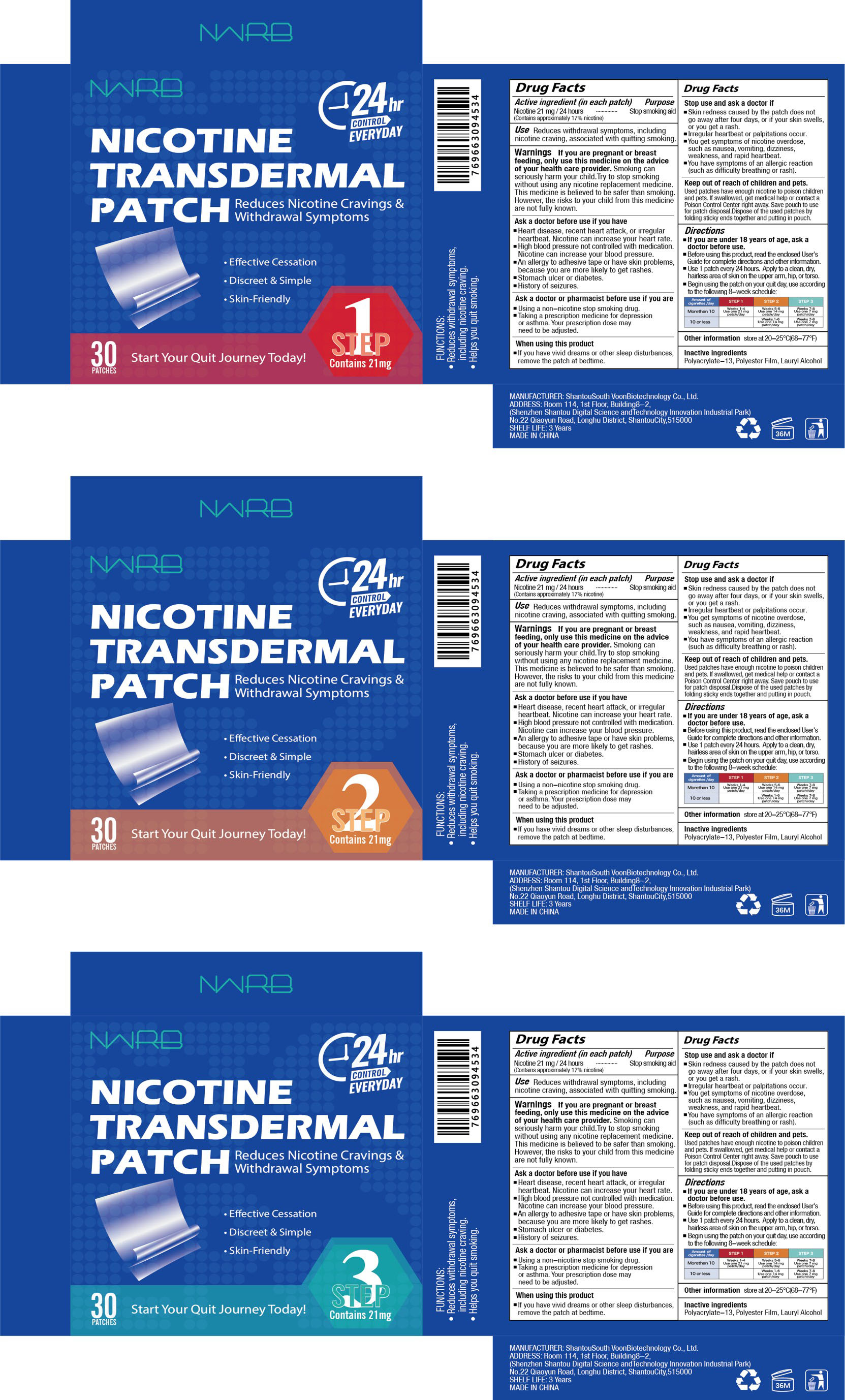 DRUG LABEL: NWRB Nicotine Transdermal Patch
NDC: 84288-007 | Form: PATCH
Manufacturer: Dongkou County Hecheng Network Technology Co., Ltd.
Category: otc | Type: HUMAN OTC DRUG LABEL
Date: 20251202

ACTIVE INGREDIENTS: NICOTINE 21 mg/1 1
INACTIVE INGREDIENTS: LAURYL ALCOHOL; POLYETHYLENE TEREPHTHALATE (INTRINSIC VISCOSITY 0.60-0.70); POLYACRYLATE-13

84288-007 NWRB Nicotine Transdermal Patch

ACTIVE INGREDIENT

Nicotine 21mg

PURPOSE

Stop smoking aid

INDICATIONS AND USAGE

Use Reduces withdrawal symptoms, including nicotine craving, associated with quitting smoking

WARNINGS

Warnings if you are pregnant or breast feeding, only use this medicine on the advice of your health care provider. Smoking can seriously harm your child.Try to stop smoking without using any nicotine replacement medicine.This medicine is believed to be safer than smoking However, the risks to your child from this medicine are not fully known.

DO NOT USE

Heart disease, recent heart attack, or irregular heartbeat. Nicotine can increase your heart rate.
High blood pressure not controlled with medication.Nicotine can increase your blood pressure.
An allergy to adhesive tape or have skin problems,because you are more likely to get rashes
.Stomach ulcer or diabetes.
History of seizures

WHEN USING

If you have vivid dreams or other sleep disturbances,remove the patch at bedtime.

STOP USE

Skin redness caused by the patch does not go away after four days, or if your skin swells,or you get a rash.
lrregular heartbeat or palpitations occur.
You get symptoms of nicotine overdose,such as nausea, vomiting, dizziness weakness, and rapid heartbeat.
You have symptoms of an allergic reaction(such as difficulty breathing or rash).

KEEP OUT OF REACH OF CHILDREN

Used patches have enough nicotine to poison children and pets. lf swallowed, get medical help or contact a Poison Control Center right away, Save pouch to use for patch disposal.Dispose of the used patches by folding sticky ends together and putting in pouch.

DOSAGE AND ADMINISTRATION

lf you are under 18 years of age, ask a doctor before use.
Before using this product, read the enclosed User's Guide for complete directions and other information.
Use 1 patch every 24 hours. Apply to a clean, dry,hairless area of skin on the upper arm, hip, or torso.
Begin using the patch on your quit day, use according to the following 8-week schedule.

INACTIVE INGREDIENT

Polyacrylate-13
Polyester Film
Lauryl Alcohol